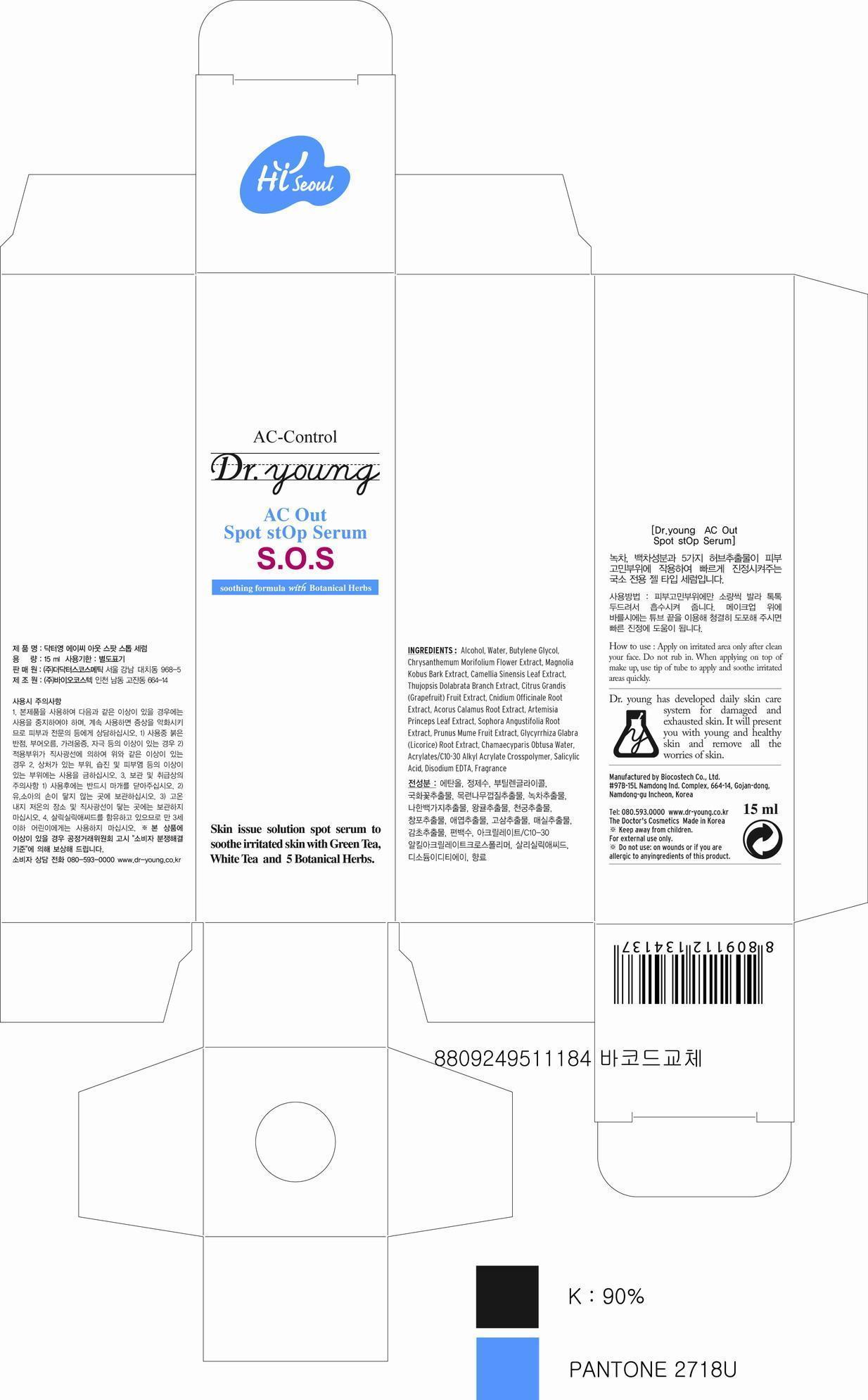 DRUG LABEL: AC Out Spot stOp Serum
NDC: 43948-1201 | Form: LIQUID
Manufacturer: The Doctors Cosmetics Co., Ltd
Category: otc | Type: HUMAN OTC DRUG LABEL
Date: 20120925

ACTIVE INGREDIENTS: SALICYLIC ACID 0.1 mg/100 mL
INACTIVE INGREDIENTS: ALCOHOL; BUTYLENE GLYCOL; CHRYSANTHEMUM X MORIFOLIUM FLOWER; MAGNOLIA KOBUS BARK; THUJOPSIS DOLABRATA LEAFY TWIG; PUMMELO; CNIDIUM OFFICINALE ROOT; ACORUS CALAMUS ROOT; ARTEMISIA PRINCEPS LEAF; SOPHORA FLAVESCENS ROOT; PRUNUS MUME FRUIT; GLYCYRRHIZA GLABRA; CHAMAECYPARIS OBTUSA WOOD OIL; CARBOMER COPOLYMER TYPE A (ALLYL PENTAERYTHRITOL CROSSLINKED)

Drug Facts

ACTIVE INGREDIENT

salicylic acid

INACTIVE INGREDIENT

water, alcohol, butylene glycol, chrysanthemum morifolium flower extract, magnolia kobus bark extract, camella sinensis leaf extract, ghujopsis dolabrata branch extract, citrus grandis fruit extract, cnidium officinale root extract, acorus calamus root extract, artemisia princeps leaf extract, sophora angustifolia root extract, prunus mume fruit extract, licorice root extract, chamaecyparis obtusa water, acrylates/c10-30 alkyl acrylate crosspolymer, disodium edta, fragrance

PURPOSE

skin proctectant

keep out of reach of the children

INDICATIONS AND USAGE

1. On clean face, only apply on troubled areas. Do not rub.

2. When applying on top of a make up, use tip of the tube

to apply and soothe troubled areas quickly

When using this product
- keep out of eyes, ears, and mouth. If contact occurs, rinse with plenty of cold water right away and contact a physician. If swallowing, drink plenty of water and contact a physician

DOSAGE AND ADMINISTRATION

for external use only